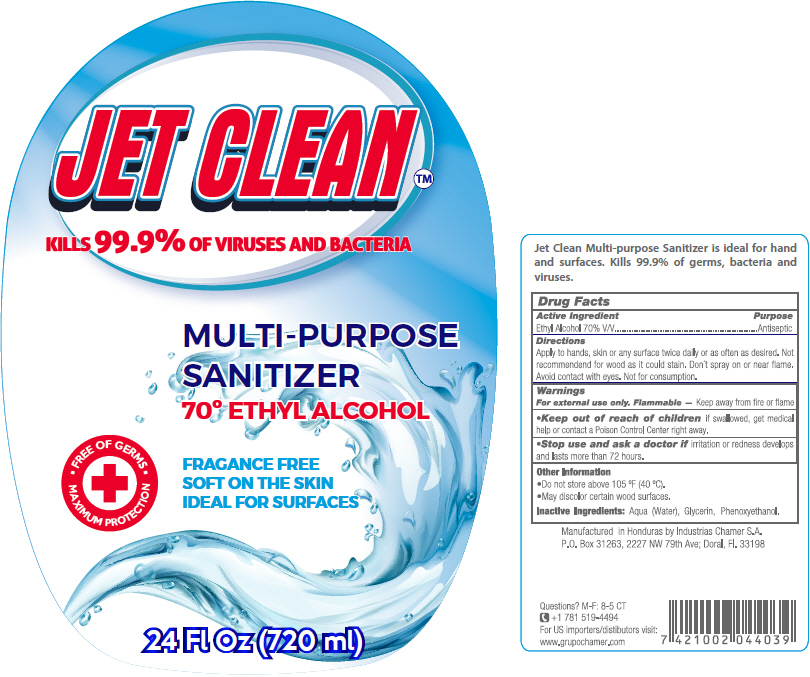 DRUG LABEL: JETCLEAN
NDC: 51774-009 | Form: LIQUID
Manufacturer: INDUSTRIAS CHAMER S.A. DE C.V.
Category: otc | Type: HUMAN OTC DRUG LABEL
Date: 20200909

ACTIVE INGREDIENTS: ALCOHOL 70 mL/100 mL
INACTIVE INGREDIENTS: WATER; GLYCERIN; PHENOXYETHANOL

JETCLEAN™

Drug Facts

Active Ingredient

Ethyl Alcohol 70% V/V

Purpose

Antiseptic

Directions

INDICATIONS AND USAGE

Apply to hands, skin or any surface twice daily or as often as desired. Not recommended for wood as it could stain. Don't spray on or near flame. Avoid contact with eyes. Not for consumption.

Warnings

For external use only. Flammable – Keep away from fire or flame

- Keep out of reach of children if swallowed, get medical help or contact a Poison Control Center right away.

- Stop use and ask a doctor if irritation or redness develops and lasts more than 72 hours.

Other Information

- Do not store above 105 °F (40 °C).
- May discolor certain wood surfaces.

Inactive Ingredients

Aqua (Water), Glycerin, Phenoxyethanol.

Questions?

M-F: 8-5 CT
+1 781 519-4494

PRINCIPAL DISPLAY PANEL - 720 ml Bottle Label

JET CLEAN™

KILLS 99.9% OF VIRUSES AND BACTERIA

MULTI-PURPOSE
SANITIZER
70° ETHYL ALCOHOL

FREE OF GERMS
MAXIMUM PROTECTION

FRAGANCE FREE
SOFT ON THE SKIN
IDEAL FOR SURFACES

24 Fl Oz (720 ml)